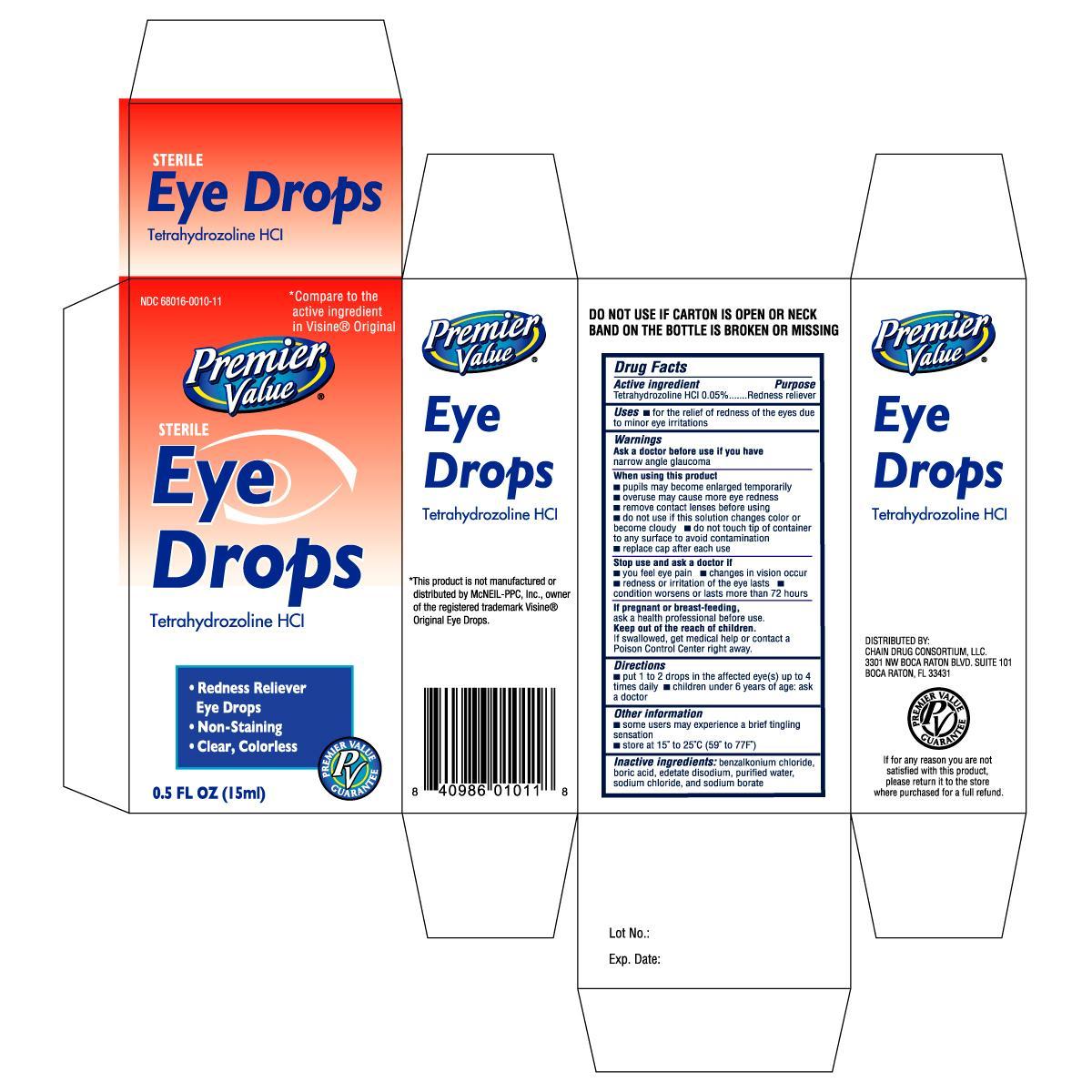 DRUG LABEL: PREMIER VALUE ORIGINAL
NDC: 11716-0101 | Form: SOLUTION
Manufacturer: HANLIM PHARM. CO., LTD.
Category: otc | Type: HUMAN OTC DRUG LABEL
Date: 20140519

ACTIVE INGREDIENTS: TETRAHYDROZOLINE HYDROCHLORIDE 0.5 mg/1 mL
INACTIVE INGREDIENTS: BENZALKONIUM CHLORIDE; BORIC ACID; EDETATE DISODIUM; WATER; SODIUM CHLORIDE; SODIUM BORATE

DRUG FACTS

Active ingredient Purpose

Tetrahydrozoline HCL 0.05%..................................Redness Reliever

Uses

- for the relief of redness of the eyes due to minor eye irritations

Ask a doctor before use if you have narrow angle glaucoma

When using this product

- pupils may become enlarged temporarily
- overuse may cause more eye redness
- remove contact lenses before using
- do not use if this solution changes color or become cloudy
- do not touch tip of container to any surface to avoid contamination
- replace cap after each use

Stop use and ask a doctor if

- you feel eye pain
- changes in vision occur
- redness or irritation of the eye lasts
- condition worsens or lasts more than 72 hours

PREGNANCY OR BREAST FEEDING

If pregnant or breast-feeding, ask a health professional before use.

Keep out of the reach of children.

If swallowed, get medical help or contact a Poison Control Center right away.

Directions

- put 1 to 2 drops in the affected eye(s) up to 4 times daily
- children under 6 years of age: ask a doctor

Other information

- some users may experience a brief tingling sensation
- store at 15o to 25oC (59o to 77oF)

INACTIVE INGREDIENT

Inactive ingredients: benzalkonium chloride, boric acid, edetate disodium, purified water, sodium chloride, and sodium borate

DOSAGE AND ADMINISTRATION

Distributed By:

Chain Drug Consortium, LLC.

3301 NW Boca Raton Blvd.

Suite 101

Boca Raton, FL 33431

PACKAGE LABEL

Enter section text here